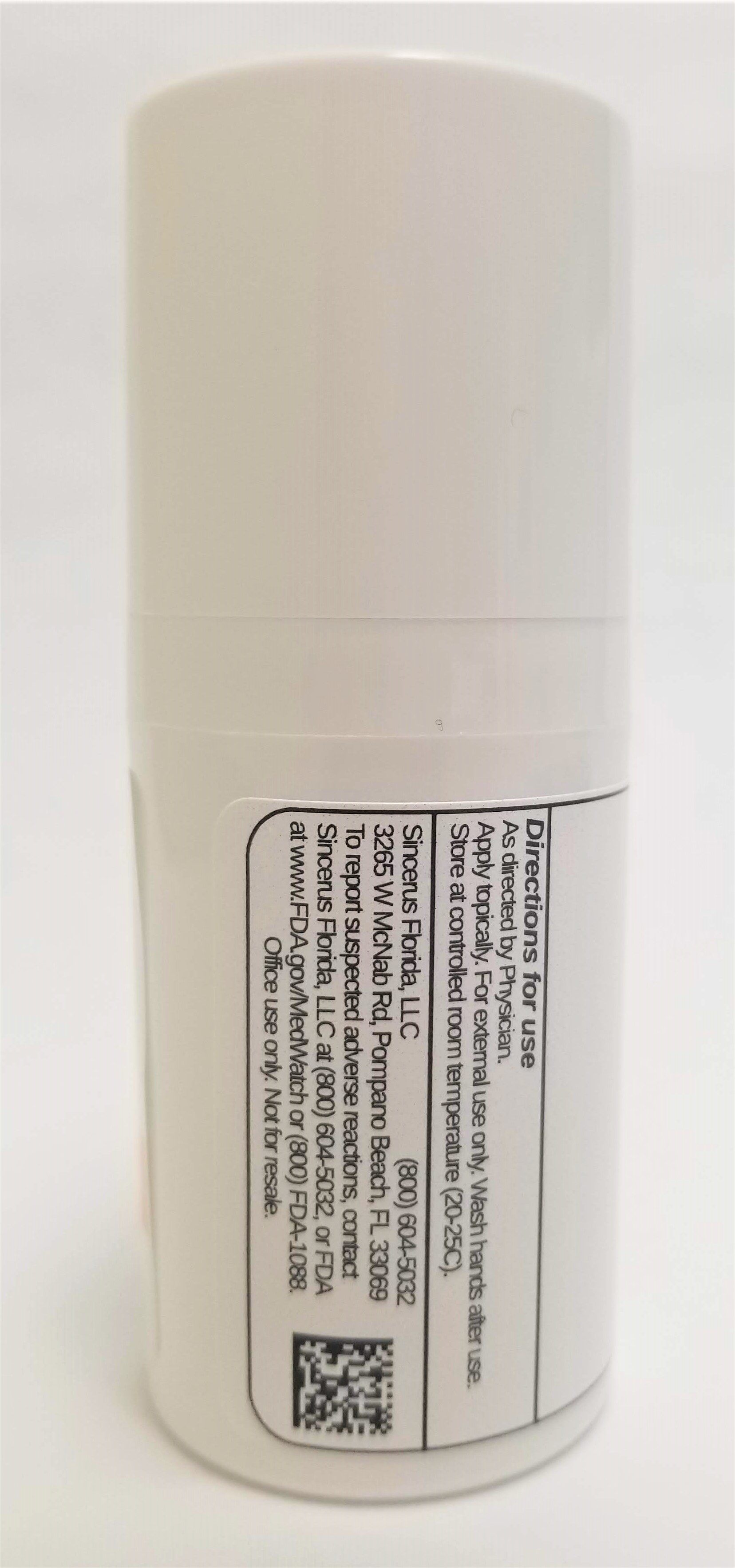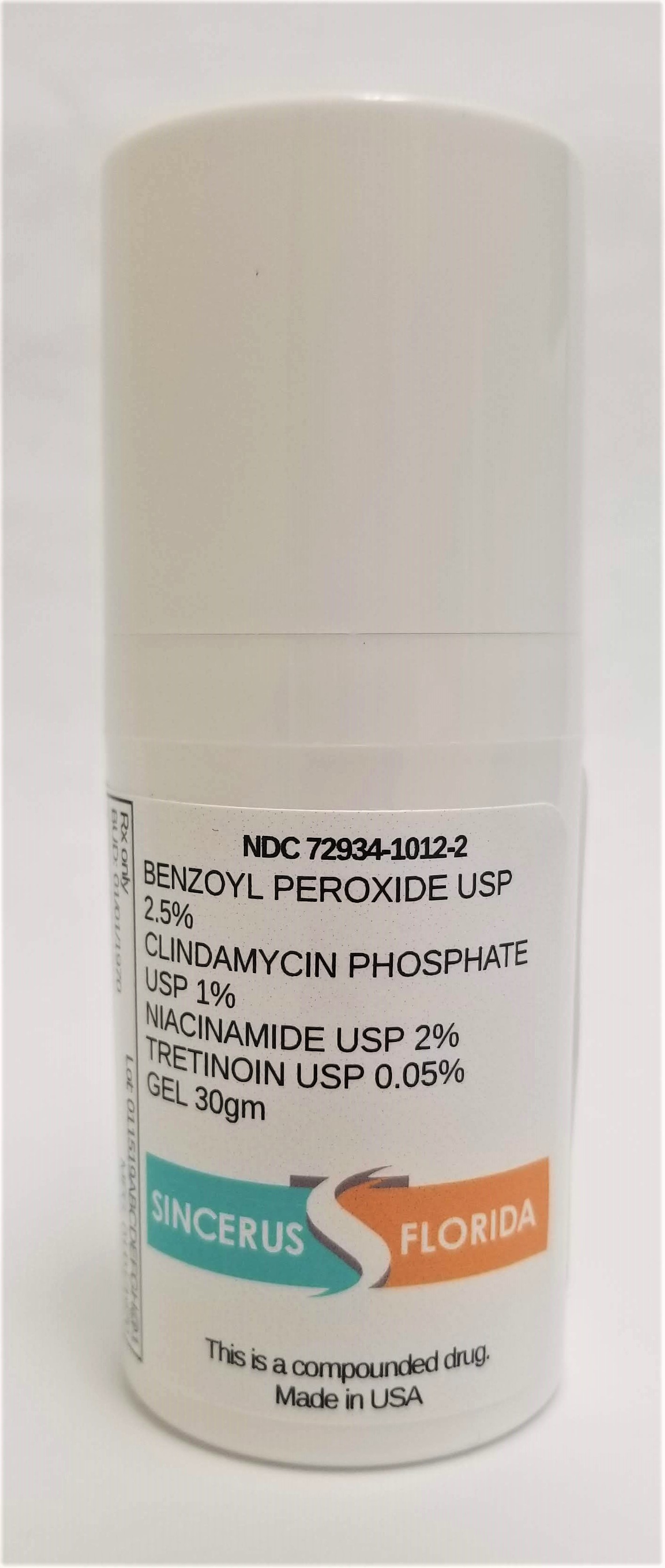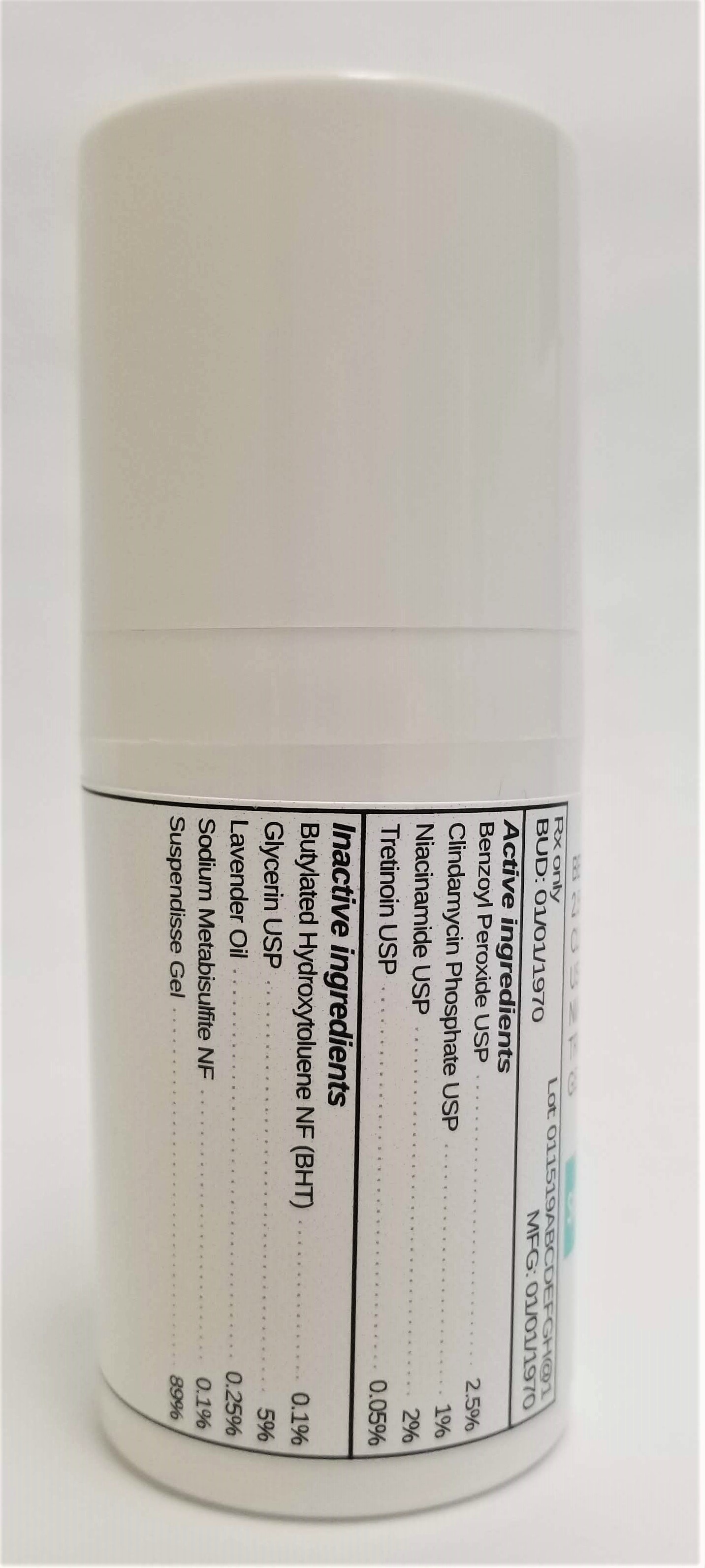 DRUG LABEL: BENZOYL PEROXIDE 2.5%, CLINDAMYCIN PHOSPHATE  1%, NIACINAMIDE 2% / TRETINOIN 0.05%
NDC: 72934-1012 | Form: GEL
Manufacturer: Sincerus Florida, LLC
Category: prescription | Type: HUMAN PRESCRIPTION DRUG LABEL
Date: 20190503

ACTIVE INGREDIENTS: NIACINAMIDE 2 g/100 g; TRETINOIN 0.05 g/100 g; CLINDAMYCIN PHOSPHATE 1 g/100 g; BENZOYL PEROXIDE 2.5 g/100 g

BENZOYL PEROXIDE USP 2.5%, CLINDAMYCIN PHOSPHATE USP 1%, NIACINAMIDE USP 2% / TRETINOIN USP 0.05%. Gel 30gm